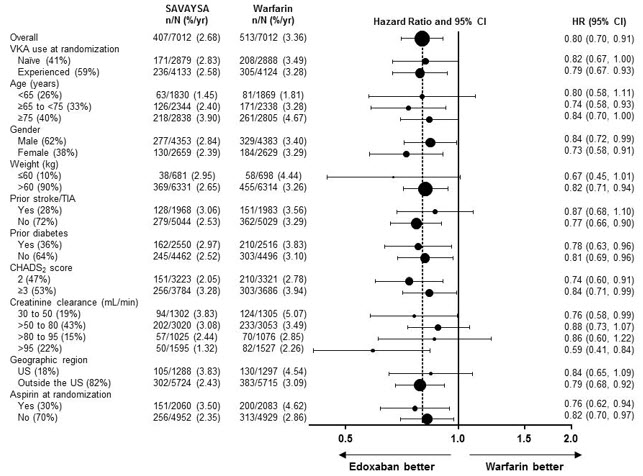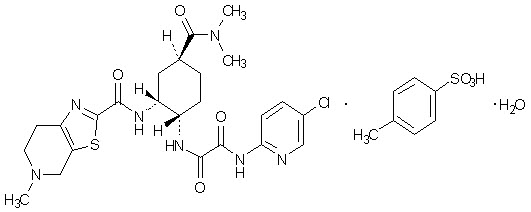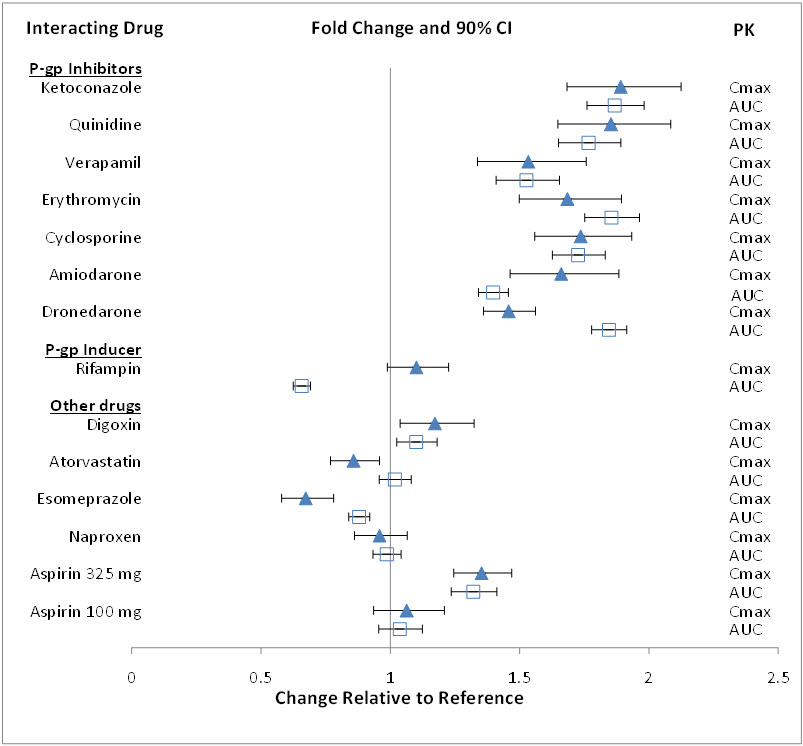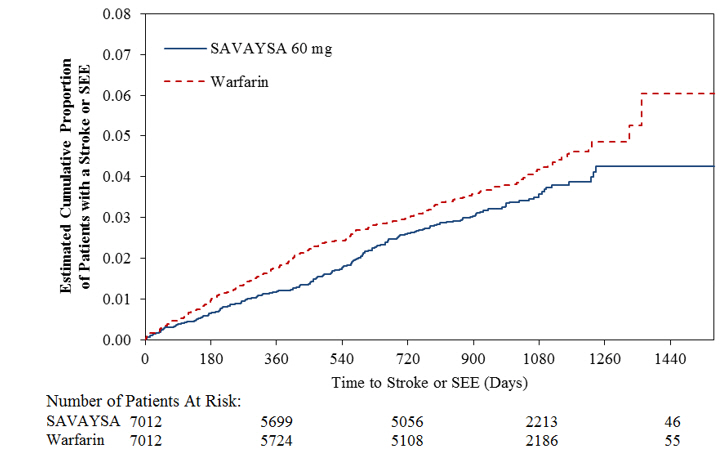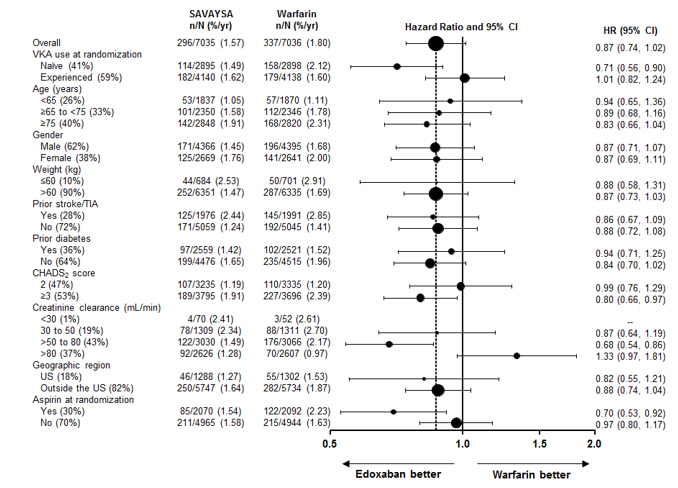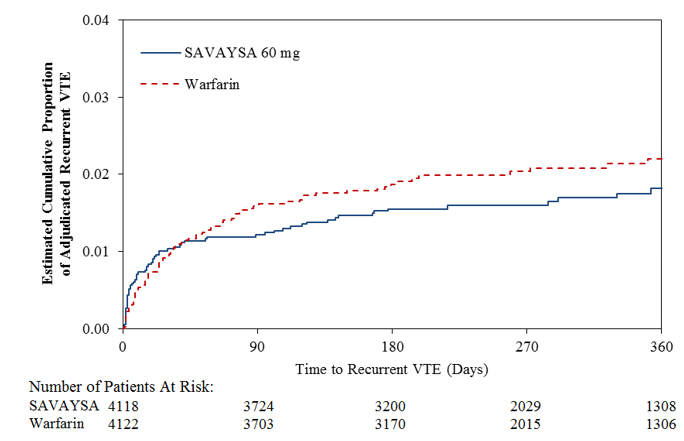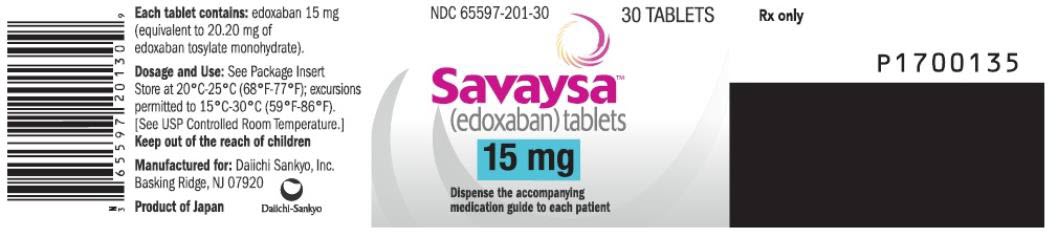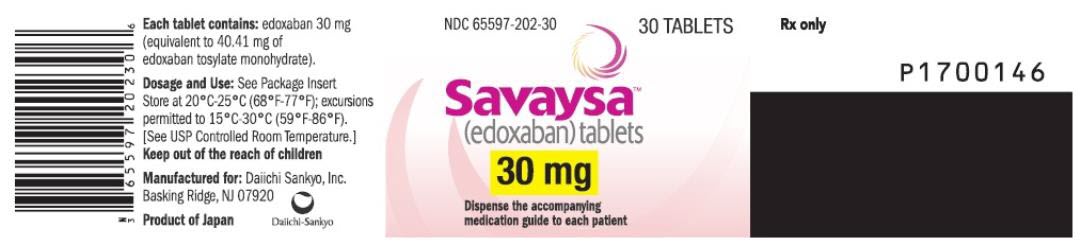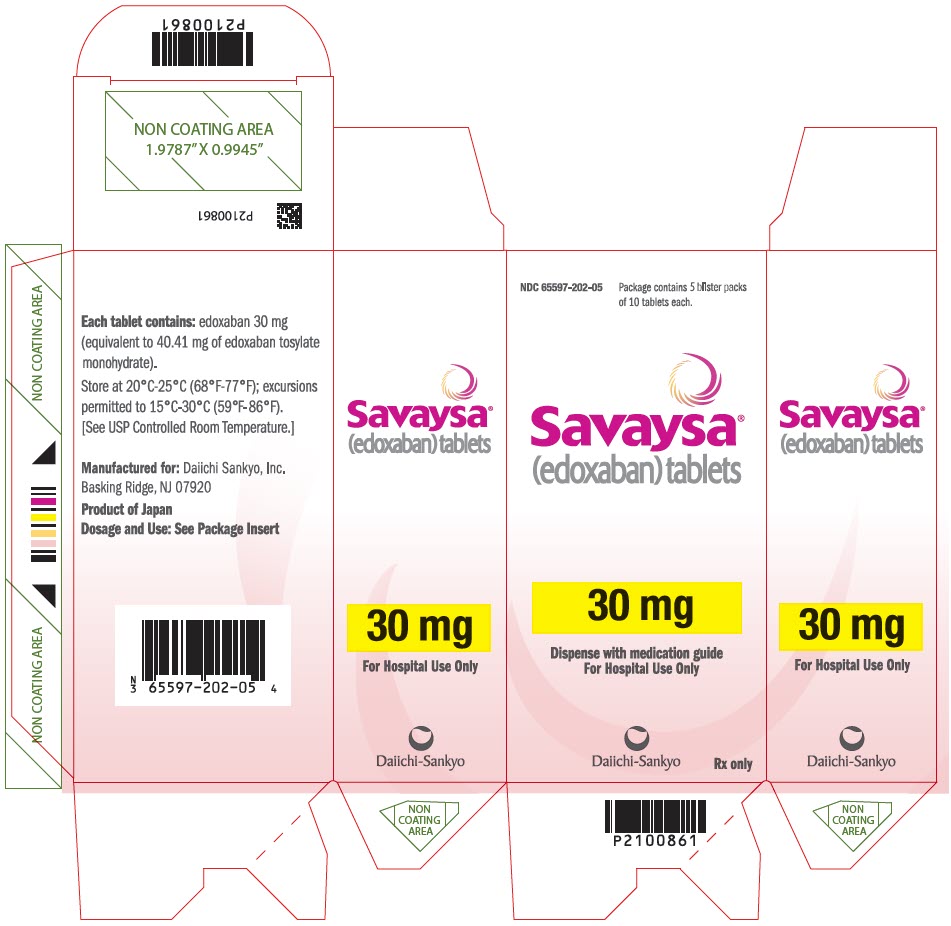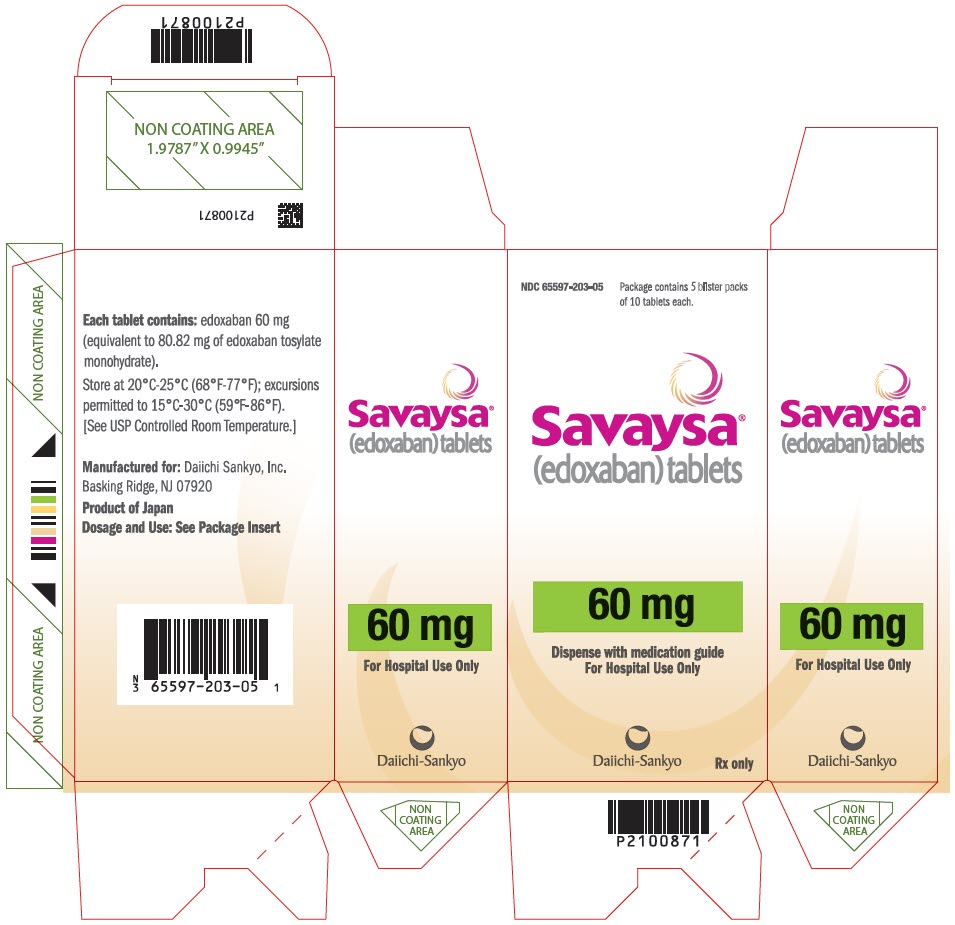 DRUG LABEL: SAVAYSA
NDC: 65597-201 | Form: TABLET, FILM COATED
Manufacturer: Daiichi Sankyo Inc.
Category: prescription | Type: HUMAN PRESCRIPTION DRUG LABEL
Date: 20250710

ACTIVE INGREDIENTS: EDOXABAN TOSYLATE 15 mg/1 1

HIGHLIGHTS OF PRESCRIBING INFORMATION

These highlights do not include all the information needed to use SAVAYSA safely and effectively. See full prescribing information for SAVAYSA.
SAVAYSA® (edoxaban) tablets, for oral use
Initial U.S. Approval: 2015

WARNING: (A) REDUCED EFFICACY IN NONVALVULAR ATRIAL FIBRILLATION PATIENTS WITH CREATININE CLEARANCE (CRCL) > 95 ML/MIN (B) PREMATURE DISCONTINUATION OF SAVAYSA INCREASES THE RISK OF ISCHEMIC EVENTS (C) SPINAL/EPIDURAL HEMATOMA

See full prescribing information for complete boxed warning.

(A) REDUCED EFFICACY IN NONVALVULAR ATRIAL FIBRILLATION PATIENTS WITH CRCL > 95 ML/MIN: SAVAYSA should not be used in patients with CrCL > 95 mL/min. In the ENGAGE AF-TIMI 48 study, nonvalvular atrial fibrillation patients with CrCL > 95 mL/min had an increased rate of ischemic stroke with SAVAYSA 60 mg once daily compared to patients treated with warfarin. In these patients another anticoagulant should be used (5.1).

(B) PREMATURE DISCONTINUATION OF SAVAYSA INCREASES THE RISK OF ISCHEMIC EVENTS: Premature discontinuation of any oral anticoagulant in the absence of adequate alternative anticoagulation increases the risk of ischemic events. If SAVAYSA is discontinued for a reason other than pathological bleeding or completion of a course of therapy, consider coverage with another anticoagulant as described in the transition guidance (2.4, 5.2, 14).

(C) SPINAL/EPIDURAL HEMATOMA: Epidural or spinal hematomas may occur in patients treated with SAVAYSA who are receiving neuraxial anesthesia or undergoing spinal puncture. These hematomas may result in long-term or permanent paralysis. Consider these risks when scheduling patients for spinal procedures (5.4).

1 INDICATIONS AND USAGE

SAVAYSA is a factor Xa inhibitor indicated:

To reduce the risk of stroke and systemic embolism (SE) in patients with nonvalvular atrial fibrillation (NVAF) (1.1)

- Limitation of Use for NVAF
  SAVAYSA should not be used in patients with creatinine clearance (CrCL) > 95 mL/min because of increased risk of ischemic stroke compared to warfarin at the highest dose studied (60 mg) (1.1)

SAVAYSA is indicated for the treatment of deep vein thrombosis (DVT) and pulmonary embolism (PE) following 5 to 10 days of initial therapy with a parenteral anticoagulant (1.2)

2 DOSAGE AND ADMINISTRATION

- Treatment of NVAF:
  Assess CrCL before initiating therapy (2.1)
  The recommended dose is 60 mg once daily in patients with CrCL >50 to ≤ 95 mL/min. Do not use SAVAYSA in patients with CrCL > 95 mL/min (2.1)
  Reduce dose to 30 mg once daily in patients with creatinine clearance 15 to 50 mL/min (2.1)

- Treatment of DVT and PE:
  The recommended dose is 60 mg once daily (2.2)
  Reduce dose to 30 mg once daily for patients with CrCL 15 to 50 mL/min or body weight less than or equal to 60 kg or who use certain P-gp inhibitors (2.2)

3 DOSAGE FORMS AND STRENGTHS

Tablets: 60 mg, 30 mg, and 15 mg (3)

4 CONTRAINDICATIONS

- Active pathological bleeding (4)

5 WARNINGS AND PRECAUTIONS

- Bleeding: Serious and potentially fatal bleeding. Promptly evaluate signs and symptoms of blood loss (5.3)
- Mechanical Heart Valves or Moderate to Severe Mitral Stenosis: Use is not recommended (5.5)
- Increased Risk of Thrombosis in Patients with Triple Positive Antiphospholipid Syndrome: SAVAYSA use not recommended. (5.6)

6 ADVERSE REACTIONS

Treatment of NVAF: The most common adverse reactions (≥ 5%) are bleeding and anemia (6.1)

Treatment of DVT and PE: The most common adverse reactions (≥ 1%) are bleeding, rash, abnormal liver function tests and anemia (6.1)

To report SUSPECTED ADVERSE REACTIONS, contact Daiichi Sankyo, Inc. at 1-877-437-7763 or FDA at 1-800-FDA-1088 or www.fda.gov/medwatch.

7 DRUG INTERACTIONS

- Anticoagulants, Antiplatelets, Thrombolytics, and Selective Serotonin Reuptake Inhibitors (SSRIs)/Serotonin Norepinephrine Reuptake Inhibitors (SNRIs): Avoid concomitant use due to increased risk of bleeding. (7.1)
- Rifampin: Avoid concomitant use (7.2)

8 USE IN SPECIFIC POPULATIONS

- Lactation: Advise not to breastfeed. (8.2)
- Impaired renal function (CrCL 15 to 50 mL/min): Reduce dose (2.1, 2.2, 8.6)
- Moderate or severe hepatic impairment: Not recommended (8.7)

FULL PRESCRIBING INFORMATION

WARNING: (A) REDUCED EFFICACY IN NONVALVULAR ATRIAL FIBRILLATION PATIENTS WITH CREATININE CLEARANCE (CRCL) > 95 ML/MIN (B) PREMATURE DISCONTINUATION OF SAVAYSA INCREASES THE RISK OF ISCHEMIC EVENTS (C) SPINAL/EPIDURAL HEMATOMA

A. REDUCED EFFICACY IN NONVALVULAR ATRIAL FIBRILLATION PATIENTS WITH CRCL > 95 ML/MIN

SAVAYSA should not be used in patients with CrCL > 95 mL/min. In the ENGAGE AF-TIMI 48 study, nonvalvular atrial fibrillation patients with CrCL > 95 mL/min had an increased rate of ischemic stroke with SAVAYSA 60 mg once daily compared to patients treated with warfarin. In these patients another anticoagulant should be used [see Dosage and Administration (2.1), Warnings and Precautions (5.1), and Clinical Studies (14.1)].

B. PREMATURE DISCONTINUATION OF SAVAYSA INCREASES THE RISK OF ISCHEMIC EVENTS

Premature discontinuation of any oral anticoagulant in the absence of adequate alternative anticoagulation increases the risk of ischemic events. If SAVAYSA is discontinued for a reason other than pathological bleeding or completion of a course of therapy, consider coverage with another anticoagulant as described in the transition guidance [see Dosage and Administration (2.4), Warnings and Precautions (5.2), and Clinical Studies (14.1)].

C. SPINAL/EPIDURAL HEMATOMA

Epidural or spinal hematomas may occur in patients treated with SAVAYSA who are receiving neuraxial anesthesia or undergoing spinal puncture. These hematomas may result in long-term or permanent paralysis. Consider these risks when scheduling patients for spinal procedures. Factors that can increase the risk of developing epidural or spinal hematomas in these patients include:

- use of indwelling epidural catheters
- concomitant use of other drugs that affect hemostasis, such as nonsteroidal anti-inflammatory drugs (NSAIDs), platelet inhibitors, other anticoagulants
- a history of traumatic or repeated epidural or spinal punctures
- a history of spinal deformity or spinal surgery
- optimal timing between the administration of SAVAYSA and neuraxial procedures is not known

[see Warnings and Precautions (5.4)].

Monitor patients frequently for signs and symptoms of neurological impairment. If neurological compromise is noted, urgent treatment is necessary [see Warnings and Precautions (5.4)].

Consider the benefits and risks before neuraxial intervention in patients anticoagulated or to be anticoagulated [see Warnings and Precautions (5.4)].

1 INDICATIONS AND USAGE

1.1 Reduction in the Risk of Stroke and Systemic Embolism in Nonvalvular Atrial Fibrillation

SAVAYSA is indicated to reduce the risk of stroke and systemic embolism (SE) in patients with nonvalvular atrial fibrillation (NVAF).

Limitation of Use for NVAF

SAVAYSA should not be used in patients with CrCL > 95 mL/min because of an increased risk of ischemic stroke compared to warfarin [see Dosage and Administration (2.1), Warnings and Precautions (5.1) and Clinical Studies (14.1)].

1.2 Treatment of Deep Vein Thrombosis and Pulmonary Embolism

SAVAYSA is indicated for the treatment of deep vein thrombosis (DVT) and pulmonary embolism (PE) following 5 to 10 days of initial therapy with a parenteral anticoagulant.

2 DOSAGE AND ADMINISTRATION

2.1 Nonvalvular Atrial Fibrillation

The recommended dose of SAVAYSA is 60 mg taken orally once daily [see Warnings and Precautions (5.1) and Clinical Studies (14.1)]. Assess creatinine clearance, as calculated using the Cockcroft-Gault equation [Cockcroft-Gault CrCL = (140-age) × (weight in kg) × (0.85 if female) / (72 × creatinine in mg/dL).] , before initiating therapy with SAVAYSA. Do not use SAVAYSA in patients with CrCL > 95 mL/min.

Reduce SAVAYSA dose to 30 mg once daily in patients with CrCL 15 to 50 mL/min [see Use in Specific Populations (8.6), and Clinical Pharmacology (12.3)].

2.2 Treatment of Deep Vein Thrombosis and Pulmonary Embolism

The recommended dose of SAVAYSA is 60 mg taken orally once daily following 5 to 10 days of initial therapy with a parenteral anticoagulant [see Clinical Studies (14.2)].

Reduce SAVAYSA dose to 30 mg once daily in patients with CrCL 15 to 50 mL/min, patients who weigh less than or equal to 60 kg, or patients who are taking certain concomitant P-gp inhibitor medications [see Clinical Studies (14.2)].

2.3 Administration Information

If a dose of SAVAYSA is missed, the dose should be taken as soon as possible on the same day. Dosing should resume the next day according to the normal dosing schedule. The dose should not be doubled to make up for a missed dose.

SAVAYSA can be taken without regard to food [see Clinical Pharmacology (12.3)].

2.4 Transition to or from SAVAYSA

Transition to SAVAYSA
From | To | Recommendation
Warfarin or other Vitamin K Antagonists | SAVAYSA | Discontinue warfarin and start SAVAYSA when the INR is ≤ 2.5
Oral anticoagulants other than warfarin or other Vitamin K Antagonists | SAVAYSA | Discontinue current oral anticoagulant and start SAVAYSA at the time of the next scheduled dose of the other oral anticoagulant
Low Molecular Weight Heparin (LMWH) | SAVAYSA | Discontinue LMWH and start SAVAYSA at the time of the next scheduled administration of LMWH
Unfractionated heparin | SAVAYSA | Discontinue the infusion and start SAVAYSA 4 hours later

Transition from SAVAYSA
From | To | Recommendation
SAVAYSA | Warfarin | Oral option: For patients taking 60 mg of SAVAYSA, reduce the dose to 30 mg and begin warfarin concomitantly. For patients receiving 30 mg of SAVAYSA, reduce the dose to 15 mg and begin warfarin concomitantly. INR must be measured at least weekly and just prior to the daily dose of SAVAYSA to minimize the influence of SAVAYSA on INR measurements. Once a stable INR ≥ 2.0 is achieved, SAVAYSA should be discontinued and the warfarin continued
SAVAYSA | Warfarin | Parenteral option: Discontinue SAVAYSA and administer a parenteral anticoagulant and warfarin at the time of the next scheduled SAVAYSA dose. Once a stable INR ≥ 2.0 is achieved the parenteral anticoagulant should be discontinued and the warfarin continued
SAVAYSA | Non-Vitamin-K-Dependent Oral anticoagulants | Discontinue SAVAYSA and start the other oral anticoagulant at the time of the next dose of SAVAYSA
SAVAYSA | Parenteral anticoagulants | Discontinue SAVAYSA and start the parenteral anticoagulant at the time of the next dose of SAVAYSA
Abbreviations: INR=International Normalized Ratio

2.5 Discontinuation for Surgery and Other Interventions

Discontinue SAVAYSA at least 24 hours before invasive or surgical procedures because of the risk of bleeding [see Warnings and Precautions (5.3)].

If surgery cannot be delayed, there is an increased risk of bleeding. This risk of bleeding should be weighed against the urgency of intervention [see Warnings and Precautions (5.3)].

SAVAYSA can be restarted after the surgical or other procedure as soon as adequate hemostasis has been established noting that the time to onset of pharmacodynamic effect is 1-2 hours [see Warnings and Precautions (5.2)]. Administer a parenteral anticoagulant and then switch to oral SAVAYSA, if oral medication cannot be taken during or after surgical intervention.

2.6 Administration Options

For patients who are unable to swallow whole tablets, SAVAYSA tablets may be crushed and mixed with 2 to 3 ounces of water and immediately administered by mouth or through a gastric tube. The crushed tablets may also be mixed into applesauce and immediately administered orally [see Clinical Pharmacology (12.3)].

3 DOSAGE FORMS AND STRENGTHS

- 60 mg, yellow round shaped, film-coated tablets, debossed with DSC L60 on one side
- 30 mg, pink round shaped, film-coated tablets, debossed with DSC L30 on one side
- 15 mg, orange round shaped, film-coated tablets, debossed with DSC L15 on one side

4 CONTRAINDICATIONS

SAVAYSA is contraindicated in patients with:

- Active pathological bleeding [see Warnings and Precautions (5.3) and Adverse Reactions (6.1)].

5 WARNINGS AND PRECAUTIONS

5.1 Reduced Efficacy in Nonvalvular Atrial Fibrillation Patients with CrCL > 95 mL/min

SAVAYSA should not be used in patients with CrCL > 95 mL/min. In the randomized ENGAGE AF-TIMI 48 study, NVAF patients with CrCL > 95 mL/min had an increased rate of ischemic stroke with SAVAYSA 60 mg daily compared to patients treated with warfarin. In these patients another anticoagulant should be used [see Dosage and Administration (2.1) and Clinical Studies (14.1)].

5.2 Increased Risk of Stroke with Discontinuation of SAVAYSA in Patients with Nonvalvular Atrial Fibrillation

Premature discontinuation of any oral anticoagulant in the absence of adequate alternative anticoagulation increases the risk of ischemic events. If SAVAYSA is discontinued for a reason other than pathological bleeding or completion of a course of therapy, consider coverage with another anticoagulant as described in the transition guidance [see Dosage and Administration (2.4) and Clinical Studies (14.1)].

5.3 Risk of Bleeding

SAVAYSA increases the risk of bleeding and can cause serious and potentially fatal bleeding. Promptly evaluate any signs or symptoms of blood loss.

Discontinue SAVAYSA in patients with active pathological bleeding.

Concomitant use of drugs affecting hemostasis may increase the risk of bleeding. These include aspirin and other antiplatelet agents, other antithrombotic agents, fibrinolytic therapy, chronic use of nonsteroidal anti-inflammatory drugs (NSAIDs), selective serotonin reuptake inhibitors (SSRIs) and serotonin norepinephrine reuptake inhibitors (SNRIs) [see Drug Interactions (7.1)].

Reversal of Anticoagulant Effect

There is no established way to reverse the anticoagulant effects of SAVAYSA, which can be expected to persist for approximately 24 hours after the last dose. The anticoagulant effect of SAVAYSA cannot be reliably monitored with standard laboratory testing. A specific reversal agent for edoxaban is not available. Hemodialysis does not significantly contribute to edoxaban clearance [see Clinical Pharmacology (12.3)]. Protamine sulfate, vitamin K, and tranexamic acid are not expected to reverse the anticoagulant activity of SAVAYSA. The use of prothrombin complex concentrates (PCC), or other procoagulant reversal agents such as activated prothrombin complex concentrate (APCC) or recombinant factor VIIa (rFVIIa) may be considered but has not been evaluated in clinical outcome studies [see Clinical Pharmacology (12.2)]. When PCCs are used, monitoring for anticoagulation effect of edoxaban using clotting test (PT, INR, or aPTT) or anti-FXa activity is not useful and is not recommended.

5.4 Spinal/Epidural Anesthesia or Puncture

When neuraxial anesthesia (spinal/epidural anesthesia) or spinal/epidural puncture is employed, patients treated with antithrombotic agents for prevention of thromboembolic complications are at risk of developing an epidural or spinal hematoma, which can result in long-term or permanent paralysis.

The risk of these events may be increased by the postoperative use of indwelling epidural catheters or the concomitant use of medicinal products affecting hemostasis. Indwelling epidural or intrathecal catheters should not be removed earlier than 12 hours after the last administration of SAVAYSA. The next dose of SAVAYSA should not be administered earlier than 2 hours after the removal of the catheter. The risk may also be increased by traumatic or repeated epidural or spinal puncture.

Monitor patients frequently for signs and symptoms of neurological impairment (e.g., numbness or weakness of the legs, bowel, or bladder dysfunction). If neurological compromise is noted, urgent diagnosis and treatment is necessary. Prior to neuraxial intervention the physician should consider the potential benefit versus the risk in anticoagulated patients or in patients to be anticoagulated for thromboprophylaxis.

5.5 Patients with Mechanical Heart Valves or Moderate to Severe Mitral Stenosis

The safety and efficacy of SAVAYSA has not been studied in patients with mechanical heart valves or moderate to severe mitral stenosis. The use of SAVAYSA is not recommended in these patients [see Clinical Studies (14.1)].

5.6 Increased Risk of Thrombosis in Patients with Triple Positive Antiphospholipid Syndrome

Direct-acting oral anticoagulants (DOACs), including SAVAYSA, are not recommended for use in patients with triple positive antiphospholipid syndrome (APS). For patients with APS (especially those who are triple positive [positive for lupus anticoagulant, anticardiolipin antibodies, and anti-beta 2-glycoprotein I antibodies]), treatment with DOACs has been associated with increased rates of recurrent thrombotic events compared with vitamin K antagonist therapy.

6 ADVERSE REACTIONS

The following clinically significant adverse reactions are discussed in greater detail in other sections of the prescribing information.

- Increased Risk of Stroke with Discontinuation of SAVAYSA in Patients with Nonvalvular Atrial Fibrillation [see Warnings and Precautions (5.2)]
- Risk of Bleeding [see Warnings and Precautions (5.3)]
- Spinal/Epidural Anesthesia or Puncture [see Warnings and Precautions (5.4)]

6.1 Clinical Trials Experience

Because clinical trials are conducted under widely varying conditions, adverse reaction rates observed in the clinical trials of a drug cannot be directly compared to rates in the clinical trials of another drug and may not reflect the rates observed in practice.

The safety of SAVAYSA was evaluated in the ENGAGE AF-TIMI 48, Hokusai VTE, and Hokusai VTE Cancer studies including 11,530 patients exposed to SAVAYSA 60 mg and 7124 patients exposed to SAVAYSA 30 mg once daily [see Clinical Studies (14)].

The ENGAGE AF-TIMI 48 Study

In the ENGAGE AF-TIMI 48 study, the median study drug exposure for the SAVAYSA and warfarin treatment groups was 2.5 years.

Bleeding was the most common reason for treatment discontinuation. Bleeding led to treatment discontinuation in 3.9% and 4.1% of patients in the SAVAYSA 60 mg and warfarin treatment groups, respectively.

In the overall population, major bleeding was lower in the SAVAYSA group compared to the warfarin group [HR 0.80 (0.70, 0.91), p < 0.001]. Table 6.1 shows major bleeding events (percentage of patients with at least one bleeding event, per year) for the indicated population (CrCL ≤ 95 mL/min).

Table 6.1: Adjudicated Bleeding Events for NVAF Patients with CrCL ≤ 95 mL/min [The on-treatment period is during treatment or within 2 days of stopping study treatment. The difference in hemorrhagic stroke rate from Table 14.1 is because Table 14.1 includes events occurring during treatment or within 3 days of stopping study treatment and this table only includes patients with CrCL ≤ 95 mL/min.]
Event [A subject can be included in multiple sub-categories if he/she had an event for those categories.] | SAVAYSA 60 mg [Includes all patients with CrCL ≤ 95 mL/min randomized to receive 60 mg once daily, including those who were dose-reduced to 30 mg once daily because of prespecified baseline conditions.] N = 5417 n (%/year) | Warfarin N = 5485 n (%/year) | SAVAYSA 60 mg vs. Warfarin HR (95% CI)
Major Bleeding [A major bleeding event (the study primary safety endpoint) was defined as clinically overt bleeding that met one of the following criteria: fatal bleeding; symptomatic bleeding in a critical site such as retroperitoneal, intracranial, intraocular, intraspinal, intra-articular, pericardial, or intramuscular with compartment syndrome; a clinically overt bleeding event that caused a fall in hemoglobin of at least 2.0 g/dL (or a fall in hematocrit of at least 6.0% in the absence of hemoglobin data), when adjusted for transfusions (1 unit of transfusion = 1.0 g/dL drop in hemoglobin).] | 357 (3.1) | 431 (3.7) | 0.84 (0.73, 0.97)
Intracranial Hemorrhage (ICH) [ICH includes primary hemorrhagic stroke, subarachnoid hemorrhage, epidural/subdural hemorrhage, and ischemic stroke with major hemorrhagic conversion.] | 53 (0.5) | 122 (1.0) | 0.44 (0.32, 0.61)
Hemorrhagic Stroke | 33 (0.3) | 69 (0.6) | 0.49 (0.32, 0.74)
Other ICH | 20 (0.2) | 55 (0.5) | 0.37 (0.22, 0.62)
Gastrointestinal [Gastrointestinal (GI) bleeds include bleeding from upper and lower GI tract. Lower GI tract bleeding includes rectal bleeds.] | 205 (1.8) | 150 (1.3) | 1.40 (1.13, 1.73)
Fatal Bleeding [Fatal bleed is a bleeding event during the on-treatment period and adjudicated as leading directly to death within 7 days.] | 21 (0.2) | 42 (0.4) | 0.51 (0.30, 0.86)
ICH | 19 (0.2) | 36 (0.3) | 0.54 (0.31, 0.94)
Non-intracranial | 2 (< 0.1) | 6 (< 0.1) | ----
Abbreviations: HR = Hazard Ratio versus Warfarin, CI = Confidence Interval, n = number of patients with events, N = number of patients in Safety population,

The most common site of a major bleeding event was the gastrointestinal (GI) tract. Table 6.2 shows the number of and the rate at which patients experienced GI bleeding in the SAVAYSA 60 mg and warfarin treatment groups.

Table 6.2: Gastrointestinal Bleeding Events for NVAF Patients with CrCL ≤ 95 mL/min [During or within 2 days of stopping study treatment]
 | SAVAYSA N = 5417 n (%/year) | Warfarin N = 5485 n (%/year)
Major Gastrointestinal (GI) Bleeding [GI bleeding was defined by location as upper or lower GI] | 205 (1.78) | 150 (1.27)
Upper GI | 123 (1.06) | 88 (0.74)
Lower GI [Lower GI bleeding included anorectal bleeding] | 85 (0.73) | 64 (0.54)
GUSTO [GUSTO – Severe or life-threatening bleeding that caused hemodynamic compromise and requires intervention] Severe GI bleeding | 16 (0.14) | 17 (0.14)
Fatal GI bleeding | 1 (< 0.1) | 2 (< 0.1)

The rate of anemia-related adverse events was greater with SAVAYSA 60 mg than with warfarin (9.6% vs. 6.8%).

The comparative rates of major bleeding on SAVAYSA and warfarin were generally consistent among subgroups (see Figure 6.1). Bleeding rates appeared higher in both treatment arms (SAVAYSA and warfarin) in the following subgroups of patients: those receiving aspirin, those in the United States, those more than 75 years old and those with reduced renal function.

Figure 6.1: Adjudicated Major Bleeding in the ENGAGE AF-TIMI 48 [During or within 2 days of stopping study treatment] Study

Note: The figure above presents effects in various subgroups all of which are baseline characteristics and most of which were pre-specified. The 95% confidence limits that are shown do not take into account how many comparisons were made, nor do they reflect the effect of a particular factor after adjustment for all other factors. Apparent homogeneity or heterogeneity among groups should not be over-interpreted.

Other Adverse Reactions

The most common non-bleeding adverse reactions (≥ 1%) for SAVAYSA 60 mg versus warfarin were rash (4.2% vs. 4.1%), and abnormal liver function tests (4.8% vs. 4.6%), respectively.

Interstitial Lung Disease (ILD) was reported as a serious adverse event on treatment for SAVAYSA 60 mg and warfarin in 15 (0.2%) and 7 (0.1%) patients, respectively. Many of the cases in both treatment groups were confounded by the use of amiodarone, which has been associated with ILD, or by infectious pneumonia. In the overall study period, there were 5 and 0 fatal ILD cases in the SAVAYSA 60 mg and warfarin groups, respectively.

The Hokusai VTE Study

The safety of SAVAYSA in the treatment of VTE was assessed in the Hokusai VTE study. The duration of drug exposure for SAVAYSA was ≤ 6 months for 1561 (37.9%) of patients, > 6 months for 2557 (62.1%) of patients and 12 months for 1661 (40.3%) of patients.

Bleeding was the most common reason for treatment discontinuation and occurred in 1.4% and 1.4% of patients in the SAVAYSA and warfarin arms, respectively.

Bleeding in Patients with DVT and/or PE in the Hokusai VTE Study

The major safety outcome was Clinically Relevant Bleeding, defined as the composite of Major and Clinically Relevant Non-Major (CRNM) Bleeding that occurred during or within three days of stopping study treatment. The incidence of Clinically Relevant Bleeding was lower in SAVAYSA than warfarin [HR (95% CI): 0.81 (0.71, 0.94); p = 0.004].

Table 6.3 shows the number of patients experiencing bleeding events in the Hokusai VTE Study.

Table 6.3: Bleeding Events in the Hokusai VTE Study
 | SAVAYSA (N = 4118) | Warfarin (N = 4122)
Clinically Relevant Bleeding [Primary Safety Endpoint: Clinically Relevant Bleeding (composite of Major and CRNM).] (Major/CRNM), n (%) | 349 (8.5) | 423 (10.3)
Major Bleeding [A major bleeding event was defined as clinically overt bleeding that met one of the following criteria: associated with a fall in hemoglobin level of 2.0 g/dL or more, or leading to transfusion of two or more units of packed red cells or whole blood; occurring in a critical site or organ: intracranial, intraspinal, intraocular, pericardial, intra-articular, intramuscular with compartment syndrome, retroperitoneal; contributing to death.] , n (%) | 56 (1.4) | 66 (1.6)
Fatal bleeding | 2 (<0.1) | 10 (0.2)
Intracranial fatal | 0 (0.0) | 6 (0.1)
Non-fatal critical organ bleeding | 13 (0.3) | 25 (0.6)
Intracranial bleeding | 5 (0.1) | 12 (0.3)
Non-fatal non-critical organ bleeding | 41 (1.0) | 33 (0.8)
Decrease in Hb ≥ 2 g/dL | 40 (1.0) | 33 (0.8)
Transfusion of ≥ 2 units of RBC | 28 (0.7) | 22 (0.5)
CRNM Bleeding [CRNM bleeding was defined as overt bleeding not meeting the criteria for a major bleeding event but that was associated with a medical intervention, an unscheduled contact (visit or telephone call) with a physician, temporary cessation of study treatment, or associated with discomfort for the subject such as pain, or impairment of activities of daily life.] | 298 (7.2) | 368 (8.9)
Any Bleed | 895 (21.7) | 1056 (25.6)
Abbreviations: N = number of patients in the modified intent-to-treat population; n = number of events; CRNM = clinically relevant non-major

Patients with low body weight (≤ 60 kg), CrCL ≤ 50 mL/min, or concomitant use of select P-gp inhibitors were randomized to receive SAVAYSA 30 mg or warfarin. As compared to all patients who received SAVAYSA or warfarin in the 60 mg cohort, all patients who received SAVAYSA or warfarin in the 30 mg cohort (n = 1452, 17.6% of the entire study population) were older (60.1 vs 54.9 years), more frequently female (66.5% vs 37.7%), more frequently of Asian race (46.0% vs 15.6%) and had more co-morbidities (e.g., history of bleeding, hypertension, diabetes, cardiovascular disease, cancer). Clinically relevant bleeding events occurred in 58/733 (7.9%) of the SAVAYSA patients receiving 30 mg once daily and 92/719 (12.8%) of warfarin patients meeting the above criteria.

In the Hokusai VTE study, among all patients the most common bleeding adverse reactions (≥ 1%) are shown in Table 6.4.

Table 6.4: Adverse Reactions Occurring in ≥ 1% of Patients Treated in Hokusai VTE
 | SAVAYSA 60 mg (N = 4118) n (%) | Warfarin (N = 4122) n (%)
Bleeding ADRs [Adjudicated Any Bleeding by location for all bleeding event categories (including Major and CRNM)]
Vaginal [Gender specific vaginal bleeding percentage is based on number of female subjects in each treatment group] | 158 (9) | 126 (7.1)
Cutaneous soft tissue | 245 (5.9) | 414 (10)
Epistaxis | 195 (4.7) | 237 (5.7)
Gastrointestinal bleeding | 171 (4.2) | 150 (3.6)
Lower gastrointestinal | 141 (3.4) | 126 (3.1)
Oral/pharyngeal | 138 (3.4) | 162 (3.9)
Macroscopic hematuria/urethral | 91 (2.2) | 117 (2.8)
Puncture site | 56 (1.4) | 99 (2.4)
Non-Bleeding ADRs
Rash | 147 (3.6) | 151 (3.7)
Abnormal liver function tests | 322 (7.8) | 322 (7.8)
Anemia | 72 (1.7) | 55 (1.3)

Bleeding in Patients with VTE in the Hokusai VTE Cancer Study

The safety of SAVAYSA in patients with cancer and VTE was evaluated in the Hokusai VTE Cancer study [see Clinical Studies (14.2)]. The median duration of SAVAYSA exposure was 211 days (range, 2 to 423). The safety outcome was major bleeding that occurred during or within three days of stopping study treatment. The incidence of major bleeding was higher in the SAVAYSA arm than in the dalteparin arm [HR (95% CI): 2.00 (1.09, 3.66)].

Table 6.5 presents the bleeding results from the Hokusai VTE Cancer study.

Table 6.5: Bleeding Events in the Hokusai VTE Cancer Study
 | SAVAYSA (N = 522) | Dalteparin (N = 524)
Major Bleeding [A major bleeding event was defined as clinically overt bleeding that met one of the following criteria: associated with a fall in hemoglobin level of 2.0 g/dL or more, or leading to transfusion of two or more units of packed red cells or whole blood; occurring in a critical site or organ: intracranial, intraspinal, intraocular, pericardial, intra-articular, intramuscular with compartment syndrome, retroperitoneal; contributing to death.] , n (%) | 32 (6.1%) | 16 (3.1%)
Fatal bleeding | 1 (0.2%) [All events in this table, except for the fatal bleeding event on SAVAYSA, are based on adjudicated events. The fatal bleeding event on SAVAYSA was adjudicated as a major bleed; however, the adjudicated cause of death was cancer-related death.] | 2 (0.4%)
Intracranial | 0 | 1 (0.2%)
Lower gastrointestinal | 1 (0.2%) | 1 (0.2%)
Non-fatal critical organ bleeding | 5 (1%) | 6 (1.1%)
Intracranial bleeding | 2 (0.4%) | 2 (0.4%)
Non-fatal non-critical organ bleeding | 27 (5.2%) | 8 (1.5%)
Gastrointestinal | 22 (4.2%) | 4 (0.8%)
Upper gastrointestinal | 18 (3.4%) | 3 (0.6%)
Lower gastrointestinal | 3 (0.6%) | 1 (0.2%)
Decrease in Hb ≥ 2 g/dL | 28 (5.4%) | 11 (2.1%)
CRNM Bleeding [CRNM bleeding was defined as overt bleeding not meeting the criteria for a major bleeding event but that was associated with a medical intervention, an unscheduled contact (visit or telephone call) with a physician, temporary cessation of study treatment, or associated with discomfort for the subject such as pain or impairment of activities of daily life.] , n (%) | 70 (13.4%) | 48 (9.2%)
Any Bleeding, n (%) | 137 (26.2%) | 104 (19.8%)
Abbreviations: N = number of patients in the modified intent-to-treat population; n = number of events; CRNM = clinically relevant non-major

In patients with GI cancer at randomization, major bleeding occurred in 13.2% (18/136) in the SAVAYSA group and 2.4% (3/125) in the dalteparin group. In patients without GI cancer at randomization, major bleeding occurred in 3.6% (14/386) in the SAVAYSA group and 3.3% (13/399) in the dalteparin group.

6.2 Postmarketing Experience

The following adverse reactions have been identified during post-approval use of SAVAYSA. Because these reactions are reported voluntarily from a population of uncertain size, it is not always possible to reliably estimate their frequency or establish a causal relationship to drug exposure.

Blood and lymphatic system disorders: thrombocytopenia

Gastrointestinal disorders: abdominal pain

Immune system disorders: angioedema, hypersensitivity

Nervous system disorders: dizziness, headache

Renal and urinary disorders: anticoagulant-related nephropathy

Skin and subcutaneous tissue disorders: urticaria

7 DRUG INTERACTIONS

7.1 Anticoagulants, Antiplatelets, Thrombolytics, and SSRIs/SNRIs

Co-administration of anticoagulants, antiplatelet drugs, thrombolytics and SSRIs or SNRIs may increase the risk of bleeding. Promptly evaluate any signs or symptoms of blood loss if patients are treated concomitantly with anticoagulants, aspirin, other platelet aggregation inhibitors, and/or NSAIDs [see Warnings and Precautions (5.3)].

Long-term concomitant treatment with SAVAYSA and other anticoagulants is not recommended because of increased risk of bleeding [see Warnings and Precautions (5.3)]. Short term co-administration may be needed for patients transitioning to or from SAVAYSA [see Dosage and Administration (2.4)].

In clinical studies with SAVAYSA concomitant use of aspirin (low dose ≤ 100 mg/day) or thienopyridines, and NSAIDs was permitted and resulted in increased rates of Clinically Relevant Bleeding. Carefully monitor for bleeding in patients who require chronic treatment with low dose aspirin and/or NSAIDs [see Warnings and Precautions (5.3) and Clinical Pharmacology (12.3)].

As with other anticoagulants the possibility may exist that patients are at an increased risk of bleeding in case of concomitant use with SSRIs or SNRIs due to their reported effect on platelets [see Warnings and Precautions (5.3)].

7.2 P-gp Inducers

Avoid the concomitant use of SAVAYSA with rifampin [see Clinical Pharmacology (12.3)].

7.3 P-gp Inhibitors

Treatment of NVAF

Based on clinical experience from the ENGAGE AF-TIMI 48 study, dose reduction in patients concomitantly receiving P-gp inhibitors resulted in edoxaban blood levels that were lower than in patients who were given the full dose. Consequently, no dose reduction is recommended for concomitant P-gp inhibitor use [see Dosage and Administration (2.1), Clinical Pharmacology (12.3), and Clinical Studies (14.1)].

Treatment of Deep Vein Thrombosis and Pulmonary Embolism

[see Clinical Studies (14.2)]

8 USE IN SPECIFIC POPULATIONS

8.1 Pregnancy

Risk Summary

Available data about SAVAYSA use in pregnant women are insufficient to determine whether there are drug-associated risks for adverse developmental outcomes. In animal developmental studies, no adverse developmental effects were seen when edoxaban was administered orally to pregnant rats and rabbits during organogenesis at up to 16-times and 8-times, respectively, the human exposure, when based on body surface area and AUC, respectively (see Data).

The estimated background risk of major birth defects and miscarriage for the indicated population is unknown. All pregnancies have a background risk of birth defect, loss, or other adverse outcomes. In the U.S. general population, the estimated background risk of major birth defects and miscarriage in clinically recognized pregnancies is 2-4% and 15-20%, respectively.

Clinical Considerations

Disease-associated maternal and/or embryo/fetal risk

Pregnancy confers an increased risk of thromboembolism that is higher for women with underlying thromboembolic disease and certain high-risk pregnancy conditions. Published data describe that women with a previous history of venous thrombosis are at high risk for recurrence during pregnancy.

Fetal/Neonatal adverse reactions

Use of anticoagulants, including edoxaban, may increase the risk of bleeding in the fetus and neonate. Monitor neonates for bleeding [see Warnings and Precautions (5.3)].

Labor or delivery

All patients receiving anticoagulants, including pregnant women, are at risk for bleeding. SAVAYSA use during labor or delivery in women who are receiving neuraxial anesthesia may result in epidural or spinal hematomas. Consider use of a shorter acting anticoagulant as delivery approaches [see Warnings and Precautions (5.3)].

Data

Animal Data

Embryo-fetal development studies were conducted in pregnant rats and rabbits during the period of organogenesis. In rats, no malformation was seen when edoxaban was administered orally at doses up to 300 mg/kg/day, or 49 times the human dose of 60 mg/day normalized to body surface area. Increased post-implantation loss occurred at 300 mg/kg/day, but this effect may be secondary to the maternal vaginal hemorrhage seen at this dose. In rabbits, no malformation was seen at doses up to 600 mg/kg/day (49 times the human exposure at a dose of 60 mg/day when based on AUC). Embryo-fetal toxicities occurred at maternally toxic doses, and included absent or small fetal gallbladder at 600 mg/kg/day, and increased post-implantation loss, increased spontaneous abortion, and decreased live fetuses and fetal weight at doses equal to or greater than 200 mg/kg/day, which is equal to or greater than 20 times the human exposure.

In a rat pre- and post-natal developmental study, edoxaban was administered orally during the period of organogenesis and through lactation day 20 at doses up to 30 mg/kg/day, which is up to 3 times the human exposure when based on AUC. Vaginal bleeding in pregnant rats and delayed avoidance response (a learning test) in female offspring were seen at 30 mg/kg/day.

8.2 Lactation

Risk Summary

There are no data on the presence of edoxaban in human milk, or its effects on the breastfeeding infant or on milk production. Edoxaban was present in rat milk. Because of the potential for serious adverse reactions in nursing infants, including hemorrhage, advise patients that breastfeeding is not recommended during treatment with SAVAYSA.

8.3 Females and Males of Reproductive Potential

Females of reproductive potential requiring anticoagulation should discuss pregnancy planning with their physician.

The risk of clinically significant uterine bleeding, potentially requiring gynecological surgical interventions, identified with oral anticoagulants including SAVAYSA should be assessed in females of reproductive potential and those with abnormal uterine bleeding.

8.4 Pediatric Use

The safety and effectiveness of SAVAYSA have not been established in pediatric patients with confirmed VTE (PE and/or DVT). Effectiveness was not demonstrated in an adequate and well-controlled study conducted in 145 SAVAYSA-treated pediatric patients, from birth to less than 18 years of age with confirmed VTE (PE and/or DVT), treated for 3 months up to a maximum of 12 months.

8.5 Geriatric Use

Of the total patients in the ENGAGE AF-TIMI 48 study, 5182 (74%) were 65 years and older, while 2838 (41%) were 75 years and older. In Hokusai VTE, 1334 (32%) patients were 65 years and older, while 560 (14%) patients were 75 years and older. In the Hokusai VTE Cancer Study, 539 (52%) patients were 65 years and older and 176 (17%) were 75 years and older. In clinical trials the efficacy and safety of SAVAYSA in elderly (65 years or older) and younger patients were similar [see Adverse Reactions (6.1), Clinical Pharmacology (12.3), and Clinical Studies (14)].

8.6 Renal Impairment

Renal clearance accounts for approximately 50% of the total clearance of edoxaban. Consequently, edoxaban blood levels are increased in patients with poor renal function compared to those with higher renal function. Reduce SAVAYSA dose to 30 mg once daily in patients with CrCL 15-50 mL/min. There are limited clinical data with SAVAYSA in patients with CrCL < 15 mL/min; SAVAYSA is therefore not recommended in these patients. Hemodialysis does not significantly contribute to SAVAYSA clearance [see Dosage and Administration (2.1, 2.2) and Clinical Pharmacology (12.3)].

As renal function improves and edoxaban blood levels decrease, the risk for ischemic stroke increases in patients with NVAF [see Indications and Usage (1.1), Dosage and Administration (2.1), and Clinical Studies (14.1)].

8.7 Hepatic Impairment

The use of SAVAYSA in patients with moderate or severe hepatic impairment (Child-Pugh B and C) is not recommended as these patients may have intrinsic coagulation abnormalities. No dose reduction is required in patients with mild hepatic impairment (Child-Pugh A) [see Clinical Pharmacology (12.3)].

8.8 Low Body Weight Consideration for Patients Treated for DVT and/or PE

Based on the clinical experience from the Hokusai VTE study, reduce SAVAYSA dose to 30 mg in patients with body weight less than or equal to 60 kg [see Dosage and Administration (2.2) and Clinical Studies (14.2)].

10 OVERDOSAGE

A specific reversal agent for edoxaban is not available. Overdose of SAVAYSA increases the risk of bleeding.

The following are not expected to reverse the anticoagulant effects of edoxaban: protamine sulfate, vitamin K, and tranexamic acid [see Warnings and Precautions (5.3)].

Hemodialysis does not significantly contribute to edoxaban clearance [see Clinical Pharmacology (12.3)].

11 DESCRIPTION

Edoxaban, a factor Xa inhibitor, is supplied as edoxaban tosylate monohydrate. The chemical name is N-(5-Chloropyridin-2-yl)-N'-[(1S,2R,4S)-4-(N,N-dimethylcarbamoyl)-2-(5-methyl-4,5,6,7-tetrahydro[1,3]thiazolo[5,4-c]pyridine-2-carboxamido)cyclohexyl] oxamide mono (4-methylbenzenesulfonate) monohydrate. Edoxaban tosylate monohydrate has the empirical formula C24H30ClN7O4S∙C7H8O3S∙H2O representing a molecular weight of 738.27. The chemical structure of edoxaban tosylate monohydrate is:

It is a white to pale yellowish-white crystalline powder. The solubility of edoxaban tosylate (pKa 6.7) decreases with increasing pH. It is slightly soluble in water, pH 3 to 5 buffer, very slightly soluble at pH 6 to 7; and practically insoluble at pH 8 to 9.

SAVAYSA is available for oral administration as a 60 mg, 30 mg, or 15 mg round shaped, film-coated tablet, debossed with product identification markings. Each 60 mg tablet contains 80.82 mg edoxaban tosylate monohydrate equivalent to 60 mg of edoxaban. Each 30 mg tablet contains 40.41 mg edoxaban tosylate monohydrate equivalent to 30 mg of edoxaban. Each 15 mg tablet contains 20.20 mg edoxaban tosylate monohydrate equivalent to 15 mg of edoxaban. The inactive ingredients are: mannitol, pregelatinized starch, crospovidone, hydroxypropyl cellulose, magnesium stearate, talc, and carnauba wax. The color coatings contain hypromellose, titanium dioxide, talc, polyethylene glycol 8000, iron oxide yellow (60 mg tablets and 15 mg tablets), and iron oxide red (30 mg tablets and 15 mg tablets).

12 CLINICAL PHARMACOLOGY

12.1 Mechanism of Action

Edoxaban is a selective inhibitor of FXa. It does not require antithrombin III for antithrombotic activity. Edoxaban inhibits free FXa, and prothrombinase activity and inhibits thrombin-induced platelet aggregation. Inhibition of FXa in the coagulation cascade reduces thrombin generation and reduces thrombus formation.

12.2 Pharmacodynamics

As a result of FXa inhibition, edoxaban prolongs clotting time tests such as prothrombin time (PT), and activated partial thromboplastin time (aPTT). Changes observed in PT, INR, and aPTT at the expected therapeutic dose, however, are small, subject to a high degree of variability and not useful in monitoring the anticoagulant effect of edoxaban. Following oral administration, peak pharmacodynamic effects are observed within 1-2 hours, which correspond with peak edoxaban concentrations (Cmax).

Cardiac Electrophysiology

In a thorough QT study in healthy men and women aged 19-45 years, no QTc interval prolongation was observed with edoxaban (90 mg and 180 mg).

Effect of PCCs on Pharmacodynamics of SAVAYSA

There is no systematic evaluation of bleeding reversal by 4-factor prothrombin complex concentrate (PCC) products in patients who have received SAVAYSA.

Effects of PCC (50 IU/kg) on the pharmacodynamics of edoxaban were studied in healthy subjects following a punch biopsy. Following administration of a single dose of edoxaban, endogenous thrombin potential (ETP) returned to pre-edoxaban baseline levels in 0.5 hours after the initiation of a 15-minute infusion of 50 IU/kg PCC, compared to more than 24 hours with placebo. Mean ETP levels continued to increase and exceeded pre-edoxaban baseline, reaching maximum elevations (~40% over pre-edoxaban levels) at 22 hours after initiating PCC dose, which was the last observation of ETP. The clinical relevance of this ETP increase is unknown.

Pharmacodynamic Interactions

Aspirin

Co-administration of aspirin (100 mg or 325 mg) and edoxaban increased bleeding time relative to that seen with either drug alone.

NSAID (Naproxen)

Co-administration of naproxen (500 mg) and edoxaban increased bleeding time relative to that seen with either drug alone.

12.3 Pharmacokinetics

Edoxaban displays approximately dose-proportional pharmacokinetics for doses of 15 to 150 mg and 60 to 120 mg following single and repeat doses, respectively, in healthy subjects.

Absorption

Following oral administration, peak plasma edoxaban concentrations are observed within 1-2 hours. Absolute bioavailability is 62%. Food does not affect total systemic exposure to edoxaban. SAVAYSA was administered with or without food in the ENGAGE AF-TIMI 48 and Hokusai VTE trials.

Administration of a crushed 60 mg tablet, either mixed into applesauce or suspended in water and given through a nasogastric tube, showed similar exposure compared to administration of an intact tablet.

Distribution

Disposition is biphasic. The steady-state volume of distribution (Vdss) is 107 (19.9) L [mean (SD)]. In vitro plasma protein binding is approximately 55%. There is no clinically relevant accumulation of edoxaban (accumulation ratio 1.14) with once daily dosing.

Steady-state concentrations are achieved within 3 days.

Metabolism

Unchanged edoxaban is the predominant form in plasma. There is minimal metabolism via hydrolysis (mediated by carboxylesterase 1), conjugation, and oxidation by CYP3A4.

The predominant metabolite M-4, formed by hydrolysis, is human-specific and active and reaches less than 10% of the exposure of the parent compound in healthy subjects. Exposure to the other metabolites is less than 5% of exposure to edoxaban.

Elimination

Edoxaban is eliminated primarily as unchanged drug in the urine. Renal clearance (11 L/hour) accounts for approximately 50% of the total clearance of edoxaban (22 L/hour). Metabolism and biliary/intestinal excretion account for the remaining clearance. The terminal elimination half-life of edoxaban following oral administration is 10 to 14 hours.

Specific Populations

Hepatic Impairment

In a dedicated pharmacokinetic study, patients with mild or moderate hepatic impairment (classified as Child-Pugh A or Child-Pugh B) exhibited similar pharmacokinetics and pharmacodynamics to their matched healthy control group. There is no clinical experience with edoxaban in patients with severe hepatic impairment [see Use in Specific Populations (8.7)].

Renal Impairment

In a dedicated pharmacokinetic study, total systemic exposure to edoxaban for subjects with CrCL > 50 to < 80 mL/min, CrCL 30 to 50 mL/min, CrCL < 30 mL/min, or undergoing peritoneal dialysis, were increased by 32%, 74%, 72%, and 93%, respectively, relative to subjects with CrCL ≥ 80 mL/min [see Use in Specific Populations (8.6)].

Hemodialysis

A 4-hour hemodialysis session reduced total edoxaban exposure by less than 7%.

Age

In a population pharmacokinetic analysis, after taking renal function and body weight into account, age had no additional clinically significant effect on edoxaban pharmacokinetics.

Weight

In a population pharmacokinetic analysis, total exposure in patients with median low body weight (55 kg) was increased by 13% as compared with patients with median high body weight (84 kg).

Gender

In a population pharmacokinetic analysis, after accounting for body weight, gender had no additional clinically significant effect on edoxaban pharmacokinetics.

Race

In a population pharmacokinetic analysis, edoxaban exposures in Asian patients and non-Asian patients were similar.

Drug Interactions

In vitro Drug Interactions Studies

In vitro studies indicate that edoxaban does not inhibit the major cytochrome P450 enzymes (CYP1A2, 2A6, 2B6, 2C8/9, 2C19, 2D6, 2E1, or 3A4) and does not induce CYP1A2, CYP3A4 or the P-gp transporter (MDR1). In vitro data also indicate that edoxaban does not inhibit the following transporters at clinically relevant concentrations: P-gp, the organic anion transporters OAT1 or OAT3; the organic cation transporters OCT1 or OCT2; or the organic ion transporting polypeptides OATP1B1 or OATP1B3. Edoxaban is a substrate of P-gp transporter.

Impact of Other Drugs on SAVAYSA

The effect of co-administered amiodarone, cyclosporine, dronedarone, erythromycin, ketoconazole, quinidine, verapamil, and rifampin on edoxaban exposure is shown in Figure 12.1.

Figure 12.1: Summary of Drug Interaction Study Results

Impact of Edoxaban on Other Drugs

Edoxaban increased the Cmax of concomitantly administered digoxin by 28%; however, the AUC was not affected. Edoxaban had no effect on the Cmax and AUC of quinidine.

Edoxaban decreased the Cmax and AUC of concomitantly administered verapamil by 14% and 16%, respectively.

13 NONCLINICAL TOXICOLOGY

13.1 Carcinogenesis, Mutagenesis, Impairment of Fertility

Edoxaban was not carcinogenic when administered daily to mice and rats by oral gavage for up to 104 weeks. The highest dose tested (500 mg/kg/day) in male and female mice was 3 and 6 times, respectively, the human exposure (AUC) at the human dose of 60 mg/day, and the highest doses tested in male (600/400 mg/kg/day) and female (200 mg/kg/day) rats were 8 and 14 times, respectively, the human exposure at the human dose of 60 mg/day.

Edoxaban and its human-specific metabolite, M-4, were genotoxic in in vitro chromosomal aberration tests but were not genotoxic in the in vitro bacterial reverse mutation (Ames test), in in vitro human lymphocytes micronucleus test, in in vivo rat bone marrow micronucleus test, in in vivo rat liver micronucleus test, and in in vivo unscheduled DNA synthesis tests.

Edoxaban showed no effects on fertility and early embryonic development in rats at doses of up to 1000 mg/kg/day (162 times the human dose of 60 mg/day normalized to body surface area).

14 CLINICAL STUDIES

14.1 Nonvalvular Atrial Fibrillation

The ENGAGE AF-TIMI 48 Study

The ENGAGE AF-TIMI 48 (NCT00781391) study was a multi-national, double-blind, non-inferiority study comparing the efficacy and safety of two SAVAYSA treatment arms (60 mg and 30 mg) to warfarin (titrated to INR 2.0 to 3.0) in reducing the risk of stroke and systemic embolic events in patients with NVAF. The non-inferiority margin (degree of inferiority of SAVAYSA to warfarin that was to be ruled out) was set at 38%, reflecting the substantial effect of warfarin in reducing strokes. The primary analysis included both ischemic and hemorrhagic strokes.

To enter the study, patients had to have one or more of the following additional risk factors for stroke:

- a prior stroke (ischemic or unknown type), transient ischemic attack (TIA) or non-CNS systemic embolism, or
- 2 or more of the following risk factors:
  1. age ≥ 75 years,
  2. hypertension,
  3. heart failure, or
  4. diabetes mellitus

A total of 21,105 patients were randomized and followed for a median of 2.8 years and treated for a median of 2.5 years. Patients in the SAVAYSA treatment arms had their dose halved (60 mg halved to 30 mg or 30 mg halved to 15 mg) if one or more of the following clinical factors were present: CrCL ≤ 50 mL/min, low body weight (≤ 60 kg) or concomitant use of specific P-gp inhibitors (verapamil, quinidine, dronedarone). Patients on antiretroviral therapy (ritonavir, nelfinavir, indinavir, saquinavir) as well as cyclosporine were excluded from the study. Approximately 25% of patients in all treatment groups received a reduced dose at baseline, and an additional 7% were dose-reduced during the study. The most common reason for dose reduction was a CrCL ≤ 50 mL/min at randomization (19% of patients).

Patients were well balanced with respect to demographic and baseline characteristics. The percentages of patients age ≥ 75 years and ≥ 80 years were approximately 40% and 17%, respectively. The majority of patients were Caucasian (81%) and male (62%). Approximately 40% of patients had not taken a Vitamin K Antagonist (VKA) (i.e., never took a VKA or had not taken a VKA for more than 2 months).

The mean patient body weight was 84 kg (185 lbs) and 10% of patients had a body weight of ≤ 60 kg. Concomitant diseases of patients in this study included hypertension (94%), congestive heart failure (58%), and prior stroke or transient ischemic attack (28%). At baseline, approximately 30% of patients were on aspirin and approximately 2% of patients were taking a thienopyridine.

Patients randomized to the warfarin arm achieved a mean TTR (time in therapeutic range, INR 2.0 to 3.0) of 65% during the course of the study.

The primary endpoint of the study was the occurrence of first stroke (either ischemic or hemorrhagic) or of a systemic embolic event (SEE) that occurred during treatment or within 3 days from the last dose taken. In the overall results of the study, shown in Table 14.1, both treatment arms of SAVAYSA were non-inferior to warfarin for the primary efficacy endpoint of stroke or SEE. However, the 30 mg (15 mg dose-reduced) treatment arm was numerically less effective than warfarin for the primary endpoint, and was also markedly inferior in reducing the rate of ischemic stroke. Based on the planned superiority analysis (ITT, which required p < 0.01 for success), statistical superiority of the 60 mg (30 mg dose-reduced) treatment arm compared to warfarin was not established in the total study population, but there was a favorable trend [HR (99% CI): 0.87 (0.71, 1.07)].

Table 14.1: Strokes and Systemic Embolic Events in the ENGAGE AF-TIMI 48 Study (mITT, on Treatment [Includes events during treatment or within 3 days of stopping study treatment])
Events | SAVAYSA 30 mg [Includes patients dose-reduced to 15 mg for the 30 mg treatment group and 30 mg for the 60 mg treatment group] (N = 7002) n (%/yr) [The event rate (%/yr) is calculated as number of events/subject-year exposure.] | SAVAYSA 60 mg (N = 7012) n (%/yr) | Warfarin (N = 7012) n (%/yr) | SAVAYSA 30 mg vs. warfarin HR (CI) [97.5% CI for primary endpoint of First Stroke or SEE. 95% CI for Ischemic Stroke, Hemorrhagic Stroke or Systemic Embolism] p-value | SAVAYSA 60 mg vs. warfarin HR (CI) p-value
First Stroke or SEE | 253 (1.6) | 182 (1.2) | 232 (1.5) | 1.07 (0.87, 1.31) p = 0.44 | 0.79 (0.63, 0.99) p = 0.017
Ischemic Stroke | 225 (1.4) | 135 (0.9) | 144 (0.9) | 1.54 (1.25, 1.90) | 0.94 (0.75, 1.19)
Hemorrhagic Stroke | 18 (0.1) | 39 (0.3) | 75 (0.5) | 0.24 (0.14, 0.39) | 0.52 (0.36, 0.77)
Systemic Embolism | 10 (< 0.1) | 8 (< 0.1) | 13 (< 0.1) | 0.75 (0.33, 1.72) | 0.62 (0.26, 1.50)
Abbreviations: HR = Hazard Ratio versus Warfarin, CI = Confidence Interval, n = number of events, mITT = Modified Intent-to-Treat, N = number of patients in mITT population, SEE = Systemic Embolic Event, yr = year.

Figure 14.1 is a plot of the time from randomization to the occurrence of the first primary endpoint in all patients randomized to 60 mg SAVAYSA or warfarin.

Figure 14.1: Kaplan-Meier Cumulative Event Rate Estimates for Primary Endpoint (first occurrence of stroke or SEE) (mITT [On-treatment Study Period defined as Initial Dose to Final Dose + three days])

The incidence rate of the primary endpoint of stroke or SEE in patients (N = 1776) treated with the 30 mg reduced dose of SAVAYSA because of a CrCL level ≤ 50 mL/min, low body weight ≤ 60 kg, or the concomitant use of a P-gp inhibitor drug, was 1.79% per year. Patients with any of these characteristics who were randomized to receive warfarin had an incidence rate of the primary endpoint of 2.21% per year [HR (95% CI): 0.81 (0.58, 1.13)].

In all randomized patients during the overall study period, the rates of CV death with SAVAYSA and warfarin were 2.74% per year vs. 3.17% per year, respectively [HR (95% CI): 0.86 (0.77, 0.97)].

The results in the ENGAGE AF-TIMI 48 study for the primary efficacy endpoint for most major subgroups are displayed in Figure 14.2.

Figure 14.2: ENGAGE AF-TIMI 48 Study: Primary Efficacy Endpoint by Subgroups (ITT Analysis Set)

Note: The figure above presents effects in various subgroups all of which are baseline characteristics and most of which were pre-specified. The 95% confidence limits that are shown do not take into account how many comparisons were made, nor do they reflect the effect of a particular factor after adjustment for all other factors. Apparent homogeneity or heterogeneity among groups should not be over-interpreted.

The results of the ENGAGE AF-TIMI 48 study show a strong relationship between the blood levels of edoxaban and its effectiveness in reducing the rate of ischemic stroke. There was a 64% increase in the ischemic stroke rate in patients in the 30 mg treatment arm (including patients with dose reduced to 15 mg) compared to the 60 mg treatment arm (including patients with dose reduced to 30 mg). Approximately half of the SAVAYSA dose is eliminated by the kidney, and edoxaban blood levels are lower in patients with better renal function, averaging about 30% less in patients with CrCL of > 80 mL/min, and 40% less in patients with CrCL > 95 mL/min when compared to patients with a CrCL of > 50 to ≤ 80 mL/min. Given the clear relationship of dose and blood levels to effectiveness in the ENGAGE AF-TIMI 48 study, it could be anticipated that patients with better renal function would show a smaller effect of SAVAYSA compared to warfarin than would patients with mildly impaired renal function, and this was in fact observed.

Table 14.2 shows the results for the study primary efficacy endpoint of first stroke or SEE as well as the effects on ischemic and hemorrhagic stroke in the pre-randomization CrCL subgroups for SAVAYSA 60 mg (including 30 mg dose-reduced) and warfarin. There was a decreased rate of ischemic stroke with SAVAYSA 60 mg compared to warfarin in patients with CrCL > 50 to ≤ 80 mL/min [HR (95% CI): 0.63 (0.44, 0.89)]. In patients with CrCL > 80 to ≤ 95 mL/min the results for ischemic stroke slightly favor warfarin with a confidence interval that crosses 1.0 [HR (95% CI): 1.11 (0.58, 2.12)]. The rate of ischemic stroke was higher relative to warfarin in the patients with CrCL > 95 mL/min [HR (95% CI): 2.16 (1.17, 3.97)]. Pharmacokinetic data indicate that patients with CrCL > 95 mL/min had lower plasma edoxaban levels, along with a lower rate of bleeding relative to warfarin than patients with CrCL ≤ 95 mL/min. Consequently, SAVAYSA should not be used in patients with CrCL > 95 mL/min [see Dosage and Administration (2.1), Warnings and Precautions (5.1), Adverse Reactions (6.1), and Clinical Pharmacology (12.3)].

In patients with CrCL ≤ 95 mL/min, the SAVAYSA 60 mg (30 mg dose-reduced) treatment arm reduced the risk of stroke or SEE when compared to warfarin [HR (95% CI): 0.68 (0.55, 0.84)].

In the indicated population (CrCL ≤ 95 mL/min), during the overall study period, the rates of CV death with SAVAYSA and warfarin were 2.95% per year vs. 3.59% per year, respectively [HR (95% CI): 0.82 (0.72, 0.93)].

Table 14.2: Primary Endpoint, Ischemic and Hemorrhagic Stroke Results in as a Function of Baseline Creatinine Clearance (mITT Population, On-Treatment)
STROKE TYPE Renal Function Subgroups [Renal function subgroups are based on estimated creatinine clearance in mL/min calculated using the Cockcroft-Gault formula.] | Treatment Arm | n (N) | Event Rate (%/yr) | SAVAYSA 60 mg vs. Warfarin HR (95% CI)
PRIMARY ENDPOINT
(STROKE/SEE)
≤ 95 (Indicated Population) | Warfarin | 211 (5485) | 1.8 | 0.68 (0.55, 0.84)
≤ 95 (Indicated Population) | SAVAYSA 60 mg | 142 (5417) | 1.2 | 0.68 (0.55, 0.84)
≤ 50 [83% of patients with pre-randomization CrCL ≤ 50 mL/min in the SAVAYSA 60 mg group were dose-reduced and consequently received SAVAYSA 30 mg daily. All patients in the warfarin group with CrCL ≤ 50 mL/min were treated in the same way as those with higher levels of CrCL.] | Warfarin | 50 (1356) | 2.0 | 0.90 (0.60, 1.34)
≤ 50 [83% of patients with pre-randomization CrCL ≤ 50 mL/min in the SAVAYSA 60 mg group were dose-reduced and consequently received SAVAYSA 30 mg daily. All patients in the warfarin group with CrCL ≤ 50 mL/min were treated in the same way as those with higher levels of CrCL.] | SAVAYSA 60 mg | 45 (1372) | 1.8 | 0.90 (0.60, 1.34)
> 50 to ≤ 80 | Warfarin | 135 (3053) | 2.0 | 0.53 (0.40, 0.70)
> 50 to ≤ 80 | SAVAYSA 60 mg | 71 (3020) | 1.1 | 0.53 (0.40, 0.70)
> 80 to ≤ 95 | Warfarin | 26 (1076) | 1.0 | 1.05 (0.61, 1.82)
> 80 to ≤ 95 | SAVAYSA 60 mg | 26 (1025) | 1.1 | 1.05 (0.61, 1.82)
> 95 [See Boxed Warning] | Warfarin | 21 (1527) | 0.6 | 1.87 (1.10, 3.17)
> 95 [See Boxed Warning] | SAVAYSA 60 mg | 40 (1595) | 1.0 | 1.87 (1.10, 3.17)
ISCHEMIC STROKE
≤ 95 (Indicated Population) | Warfarin | 129 (5485) | 1.1 | 0.80 (0.62, 1.04)
≤ 95 (Indicated Population) | SAVAYSA 60 mg | 102 (5417) | 0.9 | 0.80 (0.62, 1.04)
≤ 50 | Warfarin | 28 (1356) | 1.1 | 1.11 (0.66, 1.84)
≤ 50 | SAVAYSA 60 mg | 31 (1372) | 1.2 | 1.11 (0.66, 1.84)
> 50 to ≤ 80 | Warfarin | 83 (3053) | 1.2 | 0.63 (0.44, 0.89)
> 50 to ≤ 80 | SAVAYSA 60 mg | 52 (3020) | 0.8 | 0.63 (0.44, 0.89)
> 80 to ≤ 95 | Warfarin | 18 (1076) | 0.7 | 1.11 (0.58, 2.12)
> 80 to ≤ 95 | SAVAYSA 60 mg | 19 (1025) | 0.8 | 1.11 (0.58, 2.12)
> 95 | Warfarin | 15 (1527) | 0.4 | 2.16 (1.17, 3.97)
> 95 | SAVAYSA 60 mg | 33 (1595) | 0.9 | 2.16 (1.17, 3.97)
HEMORRHAGIC STROKE
≤ 95 (Indicated Population) | Warfarin | 70 (5485) | 0.6 | 0.50 (0.33, 0.75)
≤ 95 (Indicated Population) | SAVAYSA 60 mg | 34 (5417) | 0.3 | 0.50 (0.33, 0.75)
≤ 50 | Warfarin | 18 (1356) | 0.7 | 0.66 (0.32, 1.36)
≤ 50 | SAVAYSA 60 mg | 12 (1372) | 0.5 | 0.66 (0.32, 1.36)
> 50 to ≤ 80 | Warfarin | 45 (3053) | 0.7 | 0.38 (0.22, 0.67)
> 50 to ≤ 80 | SAVAYSA 60 mg | 17 (3020) | 0.3 | 0.38 (0.22, 0.67)
> 80 to ≤ 95 | Warfarin | 7 (1076) | 0.3 | 0.76 (0.24, 2.38)
> 80 to ≤ 95 | SAVAYSA 60 mg | 5 (1025) | 0.2 | 0.76 (0.24, 2.38)
> 95 | Warfarin | 6 (1527) | 0.2 | 0.98 (0.31, 3.05)
> 95 | SAVAYSA 60 mg | 6 (1595) | 0.2 | 0.98 (0.31, 3.05)
Abbreviations: HR = Hazard Ratio versus Warfarin, CI = Confidence Interval, n = number of events, mITT = Modified Intent-to-Treat, N = number of patients in mITT population, yr = year.

Transition to Other Anticoagulants in the ENGAGE AF-TIMI 48 Study

In the ENGAGE AF-TIMI 48 study, the schemes for transitioning from study medication to open-label warfarin at the end of study were associated with similar rates of stroke and systemic embolism in the SAVAYSA 60 mg and warfarin groups [see Dosage and Administration (2.4)]. In the SAVAYSA 60 mg group 7 (0.2%) of 4529 patients had a stroke or SEE compared to 7 (0.2%) of 4506 patients in the warfarin arm.

14.2 Treatment of Deep Vein Thrombosis and Pulmonary Embolism

The Hokusai VTE Study

SAVAYSA for the treatment of patients with deep vein thrombosis (DVT) and pulmonary embolism (PE) was studied in a multi-national, double-blind study (Hokusai VTE) (NCT00986154) which compared the efficacy and safety of SAVAYSA 60 mg orally once daily to warfarin (titrated to INR 2.0 to 3.0) in patients with acute symptomatic venous thromboembolism (VTE) (DVT or PE with or without DVT). All patients had VTE confirmed by appropriate diagnostic imaging at baseline and received initial heparin therapy with low molecular weight heparin (LMWH) or unfractionated heparin for at least 5 days [median LMWH/heparin treatment in the SAVAYSA 60 mg group was 7 days, and in the warfarin group it was 8.0 days] and until INR (sham or real) was ≥ 2.0 on two measurements. Blinded drug treatment in the warfarin arm was started concurrently with initial heparin therapy and in the SAVAYSA arm after discontinuation of initial heparin. Patients randomized to SAVAYSA received 30 mg once daily if they met one or more of the following criteria: CrCL 30 to 50 mL/min, body weight ≤ 60 kg, or concomitant use of specific P-gp inhibitors (verapamil and quinidine or the short-term concomitant administration of azithromycin, clarithromycin, erythromycin, oral itraconazole or oral ketoconazole). The edoxaban dosage regimen was to be returned to the regular dosage of 60 mg once daily at any time the subject is not taking the concomitant medication provided no other criteria for dose reduction are met. Other P-gp inhibitors were not permitted in the study. Patients on antiretroviral therapy (ritonavir, nelfinavir, indinavir, saquinavir) as well as cyclosporine were excluded from the Hokusai VTE study. The concomitant use of these drugs with SAVAYSA has not been studied in patients. The treatment duration was from 3 months up to 12 months, determined by investigator based on patient clinical features. Patients were excluded if they required thrombectomy, insertion of a caval filter, use of a fibrinolytic agent, or use of other P-gp inhibitors, had a creatinine clearance < 30 mL/min, significant liver disease, or active bleeding. The primary efficacy outcome was symptomatic VTE, defined as the composite of recurrent DVT, new non-fatal symptomatic PE, and fatal PE during the 12-month study period.

A total of 8292 patients were randomized to receive SAVAYSA or warfarin and were followed for a mean treatment duration of 252 days for SAVAYSA and 250 days for warfarin. The mean age was approximately 56 years. The population was 57% male, 70% Caucasian, 21% Asian, and about 4% Black. The presenting diagnosis was PE (with or without DVT) in 40.7% and DVT only in 59.3% of patients. At baseline, 27.6% of patients had temporary risk factors only (e.g., trauma, surgery, immobilization, estrogen therapy). Overall 9.4% had a history of cancer, 17.3% of the patients had an age ≥ 75 years and/or a body weight ≤ 50 kg, and/or a CrCL < 50 mL/min, and 31.4% of patients had NT-ProBNP ≥ 500 pg/mL.

Aspirin was taken as on treatment concomitant antithrombotic medication by approximately 9% of patients in both groups.

In the warfarin group, the median TTR (time in therapeutic range, INR 2.0 to 3.0) was 65.6%.

A total of 8240 patients (n = 4118 for SAVAYSA and n = 4122 for warfarin) received study drug and were included in the modified intent-to-treat (mITT) population. SAVAYSA was demonstrated to be non-inferior to warfarin for the primary endpoint of recurrent VTE [HR (95% CI): 0.89 (0.70, 1.13)] (Table 14.3, Figure 14.3).

Table 14.3: Primary Composite Efficacy Endpoint Results in Hokusai VTE (mITT Overall Study Period)
Primary Endpoint | SAVAYSA [Includes patients dose-reduced to 30 mg. Among the 1452 (17.6%) patients with low body weight (≤ 60 kg), moderate renal impairment (CrCL ≤ 50 mL/min), or concomitant use of P-gp inhibitors in the Hokusai VTE study, 22 (3.0%) of the SAVAYSA patients (30 mg once daily, n = 733) and 30 (4.2%) of warfarin patients (n = 719) had a symptomatic recurrent VTE event] n/N (%) | Warfarin n/N (%) | SAVAYSA vs. Warfarin HR (95% CI)
All patients with symptomatic recurrent VTE [Primary Efficacy Endpoint: Symptomatic recurrent VTE (i.e., the composite endpoint of DVT, non-fatal PE and fatal PE)] | 130/4118 (3.2) | 146/4122 (3.5) | 0.89 (0.70,1.13)
PE with or without DVT | 73/4118 (1.8) | 83/4122 (2.0) | -
Fatal PE and Death where PE cannot be ruled out | 24/4118 (0.6) | 24/4122 (0.6) | -
Non-fatal PE | 49/4118 (1.2) | 59/4122 (1.4) | -
DVT only | 57/4118 (1.4) | 63/4122 (1.5) | -
Index PE [Index PE refers to patients whose presenting diagnosis was PE (with or without concomitant DVT)] patients with symptomatic recurrent VTE | 47/1650 (2.8) | 65/1669 (3.9) | -
Index DVT [Index DVT refers to patients whose presenting diagnosis was DVT only] patients with symptomatic recurrent VTE | 83/2468 (3.4) | 81/2453 (3.3) | -
Abbreviations: mITT = modified intent-to-treat; HR =hazard ratio vs. warfarin; CI =confidence interval; N = number of patients in mITT population; n = number of events

Figure 14.3: Kaplan-Meier Cumulative Event Rate Estimates for Adjudicated Recurrent VTE (mITT analysis – on treatment)

The Hokusai VTE Cancer Study

In the Hokusai VTE Cancer study (NCT02073682), 1050 patients were randomized to receive SAVAYSA 60 mg once daily [30 mg dose reduced per the dose adjustment regimen used in Engage AF-TIMI 48 and Hokusai VTE studies, (see The Hokusai VTE Study)] after at least 5 days of low-molecular-weight heparin treatment or dalteparin (200 IU/kg day 1-30; 150 IU/kg day 31 to the end of treatment). The treatment duration was for a minimum of 6 months and up to 12 months.

The efficacy of SAVAYSA was based upon the rate of recurrent VTE (mITT) during the overall study period. SAVAYSA was non-inferior to dalteparin for the rate of recurrent VTE. Recurrent VTE occurred in 7.9% (41/522) and 11.3% (59/524) of patients in the SAVAYSA and dalteparin groups, respectively [HR (95% CI): 0.71 (0.48, 1.06)].

16 HOW SUPPLIED/STORAGE AND HANDLING

SAVAYSA (edoxaban) is supplied as round shaped, film-coated, non-scored tablets containing edoxaban tosylate equivalent to 60, 30 or 15 mg of SAVAYSA, packaged in bottles and blisters.

 |  |  | NDC 65597-xxx-yy
Strength | Color | Deboss |  | yy
Strength | Color | Deboss | xxx | Bottle of |  |  | Blister of
 |  |  |  | 30 | 90 | 500 | 10 × 10 [10 blister cards of 10 counts] | 10 × 5 [5 blister cards of 10 counts]
15 mg | orange | DSC L15 | 201 | 30 | - | - | - | -
30 mg | pink | DSC L30 | 202 | 30 | 90 | 50 | 10 | 05
60 mg | yellow | DSC L60 | 203 | 30 | 90 | 50 | 10 | 05

STORAGE AND HANDLING

Store at 20-25°C (68-77°F); excursions permitted to 15°-30°C (59°-86°F) [see USP Controlled Room Temperature].

Keep out of the reach of children.

17 PATIENT COUNSELING INFORMATION

Advise the patient to read the FDA-approved patient labeling (Medication Guide).

Advise patients of the following:

Instructions for Patient Use

- Advise patients to take SAVAYSA exactly as prescribed.
- Remind patients to not discontinue SAVAYSA without talking to the healthcare provider who prescribed it.
- Instruct patients to keep an adequate supply of tablets to ensure continuous dosing of SAVAYSA.
- Instruct patients who cannot swallow the tablet whole to crush SAVAYSA, combine with 2 to 3 ounces of water or applesauce and ingest immediately.
- Instruct patients who require a gastric tube to crush the SAVAYSA tablet and mix it with 2 to 3 ounces of water before administering immediately via the gastric feeding tube.
- Inform patients that if a dose is missed, they should take SAVAYSA as soon as possible the same day, and resume the normal dosing schedule the following day. The dose should not be doubled to make up for a missing dose.

Bleeding Risk

- Advise patients that they may bleed more easily, may bleed longer, or bruise more easily when treated with SAVAYSA.
- Instruct patients to report any unusual bleeding immediately to their healthcare provider.
- For patients that are having neuraxial anesthesia or spinal puncture, advise patients to watch for signs and symptoms of spinal or epidural hematoma, such as back pain, tingling, numbness (especially in the lower limbs), muscle weakness, and stool or urine incontinence. If any of these symptoms occur, advise the patient to contact his or her physician immediately [see Boxed Warning].

Invasive or Surgical Procedures

- Remind patients to inform their healthcare providers that they are taking SAVAYSA before any surgery, medical, or dental procedure is scheduled.

Concomitant Medication and Herbals

- Remind patients to inform their healthcare providers and dentists if they plan to take, or are taking any prescription medications, over-the-counter drugs or herbal products.

Pregnancy

- Remind patients to inform their healthcare provider immediately if they become pregnant or intend to become pregnant during treatment with SAVAYSA.
- Inform patients to not breastfeed if they are taking SAVAYSA [see Use in Specific Populations (8.2)].

Manufactured by:
Daiichi Sankyo Co., LTD.
Tokyo 103-8426
Japan

Distributed by:
Daiichi Sankyo, Inc.
Basking Ridge, NJ 07920-2311 USA
SAVAYSA® is a trademark of Daiichi Sankyo Co., LTD.
Copyright © 2023, Daiichi Sankyo, Inc.

USPI-SAV-C9-1023-r104

MEDICATION GUIDE
SAVAYSA (sa vaye' sah)
(edoxaban) tablets

What is the most important information I should know about SAVAYSA?

- For people who take SAVAYSA for nonvalvular atrial fibrillation (a type of irregular heartbeat):
  People with nonvalvular atrial fibrillation are at an increased risk of forming a blood clot in the heart, which can travel to the brain, causing a stroke, or to other parts of the body. SAVAYSA reduces your risk of having a stroke by helping to prevent clots from forming.
  - Your healthcare provider should check your kidney function before you start taking SAVAYSA. People whose kidneys work really well should not receive SAVAYSA because it may not work well to prevent stroke.
  - Do not stop taking SAVAYSA without first talking to the healthcare provider who prescribed it for you. Stopping SAVAYSA increases your risk of having a stroke.
- SAVAYSA can cause bleeding which can be serious, and sometimes lead to death. This is because SAVAYSA is a blood thinner medicine that reduces blood clotting. During treatment with SAVAYSA, you may bleed more easily, bleed longer, or bruise more easily. Call your healthcare provider or get medical help right away if you experience bleeding that is severe (for example, coughing up or vomiting blood) or bleeding that cannot be controlled.
  You may have a higher risk of bleeding if you take SAVAYSA and take other medicines that increase your risk of bleeding, including:
  - aspirin or aspirin-containing products
  - long-term (chronic) use of nonsteroidal anti-inflammatory drugs (NSAIDs)
  - long-term (chronic) use of blood thinner medicines, such as:
    - warfarin sodium (Coumadin, Jantoven)
    - any medicine that contains heparin
  - selective serotonin reuptake inhibitors (SSRIs) or serotonin norepinephrine reuptake inhibitors (SNRIs)
  - other medicines to prevent or treat blood clots
  Tell your healthcare provider if you take any of these medicines. Ask your healthcare provider or pharmacist if you are not sure if your medicine is one listed above.
- Spinal or epidural blood clots (hematoma). People who take a blood thinner medicine (anticoagulant) like SAVAYSA, and have medicine injected into their spinal and epidural area, or have a spinal puncture have a risk of forming a blood clot that can cause long-term or permanent loss of the ability to move (paralysis). Your risk of developing a spinal or epidural blood clot is higher if:
  - a thin tube called an epidural catheter is placed in your back to give you certain medicine
  - you take NSAIDs or a medicine to prevent blood from clotting
  - you have a history of difficult or repeated epidural or spinal punctures
  - you have a history of problems with your spine or have had surgery on your spine.
  If you take SAVAYSA and receive spinal anesthesia or have a spinal puncture, your healthcare provider should watch you closely for symptoms of spinal or epidural blood clots. Tell your healthcare provider right away if you have back pain, tingling, numbness (especially in your legs and feet), muscle weakness, or loss of control of the bowels or bladder (incontinence).
- SAVAYSA is not for people with mechanical heart valves or people who have moderate to severe narrowing (stenosis) of their mitral valve.
- SAVAYSA is not for use in people with antiphospholipid syndrome (APS), especially with positive triple antibody testing, who have a history of blood clots.

See "What are the possible side effects of SAVAYSA?" for more information about side effects.

What is SAVAYSA?
SAVAYSA is a prescription medicine used to:

- reduce the risk of stroke and blood clots in people who have atrial fibrillation not caused by a heart valve problem (nonvalvular atrial fibrillation).
- treat blood clots in the veins of your legs (deep vein thrombosis) or lungs (pulmonary embolism), after you have been treated with an injectable blood thinner medicine for 5 to 10 days.

It is not known if SAVAYSA is safe and effective in children with known deep vein thrombosis or pulmonary embolism.

Who should not take SAVAYSA?
Do not take SAVAYSA if you currently have certain types of abnormal bleeding.

Before taking SAVAYSA, tell your healthcare provider about all of your medical conditions, including if you:

- have liver or kidney problems
- have ever had bleeding problems
- have a mechanical heart valve
- have antiphospholipid syndrome
- have cancer of the stomach or intestine (gastrointestinal cancer)
- are pregnant or plan to become pregnant. It is not known if SAVAYSA will harm your unborn baby. Tell your healthcare provider right away if you become pregnant during treatment with SAVAYSA.
  Females who are able to become pregnant: Talk with your healthcare provider about pregnancy planning during treatment with SAVAYSA. Talk with your healthcare provider about your risk for severe uterine bleeding if you are treated with blood thinner medicines, including SAVAYSA.
- are breastfeeding or plan to breastfeed. It is not known if SAVAYSA passes into your breast milk. Do not breastfeed during treatment with SAVAYSA.

Tell all of your healthcare providers and dentists that you are taking SAVAYSA. They should talk to the healthcare provider who prescribed SAVAYSA for you, before you have any surgery, medical or dental procedure.
Tell your healthcare provider about all the medicines you take, including prescription and over-the-counter medicines, vitamins, and herbal supplements. Some of your other medicines may affect the way SAVAYSA works. Certain medicines may increase your risk of bleeding or stroke when taken with SAVAYSA. See "What is the most important information I should know about SAVAYSA?"
Know the medicines you take. Keep a list of them to show your healthcare provider and pharmacist when you get a new medicine.

How should I take SAVAYSA?

- Take SAVAYSA exactly as prescribed by your healthcare provider.
- Your healthcare provider will decide how long you should take SAVAYSA. Do not change your dose or stop taking SAVAYSA unless your healthcare provider tells you to. If you are taking SAVAYSA for nonvalvular atrial fibrillation, stopping SAVAYSA may increase your risk of having a stroke.
- Take SAVAYSA with or without food.
- If you have difficulty swallowing the tablet whole, talk to your healthcare provider about other ways to take SAVAYSA.
- If you miss a dose of SAVAYSA, take it as soon as you remember on the same day. Take your next dose at your usual time the next day. Do not take more than one dose of SAVAYSA at the same time to make up for a missed dose.
- Do not run out of SAVAYSA. Refill your prescription before you run out. If you take too much SAVAYSA, go to the nearest hospital emergency room or call your healthcare provider right away.
- Call your healthcare provider right away if you fall or injure yourself, especially if you hit your head. Your healthcare provider may need to check you.

What are the possible side effects of SAVAYSA?
SAVAYSA can cause serious side effects.
See "What is the most important information I should know about SAVAYSA?"
The most common side effects in people who take SAVAYSA for nonvalvular atrial fibrillation include bleeding and low red blood cell count (anemia).
The most common side effects in people who take SAVAYSA for deep vein thrombosis and pulmonary embolism include bleeding, rash, abnormal liver function tests, and low red blood cell count (anemia).
Call your doctor for medical advice about side effects. You may report side effects to FDA at 1-800-FDA-1088.

How should I store SAVAYSA?

- Store SAVAYSA at room temperature between 68°F to 77°F (20°C to 25°C).

Keep SAVAYSA and all medicines out of the reach of children.

General information about the safe and effective use of SAVAYSA
Medicines are sometimes prescribed for purposes other than those listed in a Medication Guide. Do not use SAVAYSA for a condition for which it was not prescribed. Do not give SAVAYSA to other people, even if they have the same symptoms that you have. It may harm them. You can ask your pharmacist or healthcare provider for information about SAVAYSA that is written for health professionals.

What are the ingredients in SAVAYSA?
Active ingredient: edoxaban tosylate monohydrate
Inactive ingredients: mannitol, pregelatinized starch, crospovidone, hydroxypropyl cellulose, magnesium stearate, talc, and carnauba wax. The color coatings contain hypromellose, titanium dioxide, talc, polyethylene glycol 8000, iron oxide yellow (60 mg tablets and 15 mg tablets), and iron oxide red (30 mg tablets and 15 mg tablets).
Manufactured by: Daiichi Sankyo Co., LTD., Tokyo 103-8426, Japan
Distributed by: Daiichi Sankyo, Inc., Basking Ridge, NJ 07920-2311 USA
The brands listed above are trademarks of their respective owners.
Copyright© 2023, Daiichi Sankyo, Inc.
USMG-SAV-C9-1023-r103
For more information, call 1-877-437-7763 or go to https://savaysa.com.

This Medication Guide has been approved by the U.S. Food and Drug Administration.

Revised: 10/2023

PACKAGE LABEL

PRINCIPAL DISPLAY PANEL

NDC 65597-201-30
Savaysa
(edoxaban) tablets
15 mg
30 TABLETS
Rx Only

PRINCIPAL DISPLAY PANEL

NDC 65597-202-30
Savaysa
(edoxaban) tablets
30 mg
30 TABLETS
Rx Only

PRINCIPAL DISPLAY PANEL - 30 mg Blister Pack Carton

NDC 65597-202-05
Package contains 5 blister packs
of 10 tablets each.

Savaysa®
(edoxaban) tablets

30 mg

Dispense with medication guide
For Hospital Use Only

Daiichi-Sankyo

Rx only

PRINCIPAL DISPLAY PANEL - 60 mg Blister Pack Carton

NDC 65597-203-05
Package contains 5 blister packs
of 10 tablets each.

Savaysa®
(edoxaban) tablets

60 mg

Dispense with medication guide
For Hospital Use Only

Daiichi-Sankyo

Rx only